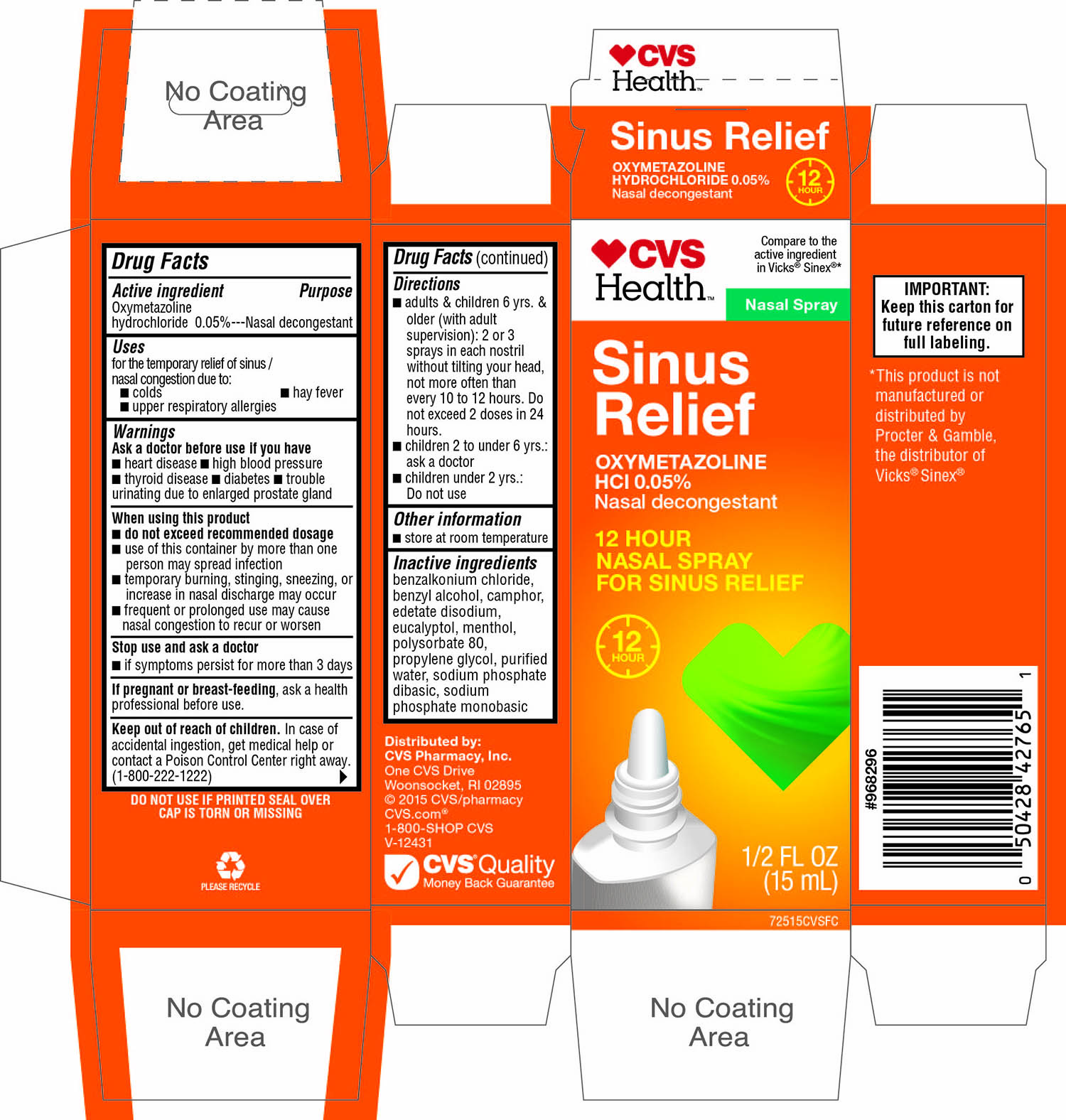 DRUG LABEL: CVS Health Sinus Relief
NDC: 59779-787 | Form: SPRAY
Manufacturer: CVS Pharmacy,Inc.
Category: otc | Type: HUMAN OTC DRUG LABEL
Date: 20161102

ACTIVE INGREDIENTS: OXYMETAZOLINE HYDROCHLORIDE 0.00050 g/1 mL
INACTIVE INGREDIENTS: BENZALKONIUM CHLORIDE; BENZYL ALCOHOL; CAMPHOR (NATURAL); EDETATE DISODIUM; EUCALYPTOL; MENTHOL; POLYSORBATE 80; PROPYLENE GLYCOL; SODIUM PHOSPHATE, DIBASIC, ANHYDROUS; SODIUM PHOSPHATE, MONOBASIC, ANHYDROUS; WATER

CVS Health™ Sinus Relief OXYMETAZOLINE HCl 0.05% 12 Hour Nasal Spray

Active ingredient

Oxymetazoline hydrochloride 0.05%

Purpose

Nasal Decongestant

Uses

- for the temporary relief of sinus/ nasal congestion due to:
- colds
- hay fever
- upper respiratory allergies

Warnings

Ask a doctor before use if you have

- heart disease
- high blood pressure
- thyroid disease
- diabetes
- trouble urinating due to enlarged prostate gland

When using this product

- do not exceed recommended dosage
- use of this container by more than one person may spread infection.
- temporary burning, stinging, sneezing or increase in nasal discharge may occur
- frequent or prolonged use may cause nasal congestion to recur or worsen

Stop use and ask a doctor

If Symptoms persist for more than 3 days

If pregnant or breast-feeding,

ask a health professional before use.

Keep out of reach of children.

In case of accidental ingestion, get medical help or contact a Poison Control Center right away. (1-800-222-1222)

Directions

- adults and children 6 yrs, & older (with adult supervision): 2 or 3 sprays in each nostril without tilting your head, not more often than every 10 to 12 hours. Do not exceed 2 doses in any 24 hours.
- children 2 to under 6 yrs : ask a doctor
- children under 2 yrs: Do not use

Other information

- store at room temperature

Inactive ingredients

benzalkonium chloride, benzyl alcohol, camphor, edetate disodium, eucalyptol, menthol, polysorbate 80,propylene glycol, purified water, sodium phosphate dibasic, sodium phosphate monobasic

Principal Display Panel

CVS Health ™

Compare to the active ingredient in Vicks® Sinex® *

Nasal Spray

Sinus Relief

OXYMETAZOLINE HCl 0.05%

Nasal decongestant

12 HOUR

NASAL SPRAY FOR SINUS RELIEF

12 Hour

1/2 FL OZ (15 mL)

DO NOT USE IF PRINTED SEAL OVER CAP IS TORN OR MISSNG

IMPORTANT: Keep this carton for future reference on full labeling.

*This product is not manufactured or distributed by Procter & Gamble, the distributor of Vicks®Sinex®

Distributed by:

CVS Pharmacy, Inc.

One CVS Drive

Woonsocket, RI 02895

© 2015 CVS/pharmacy

CVS.com®

1-800-SHOP CVS

V-12431

CVS Quality

Money Back Guarantee